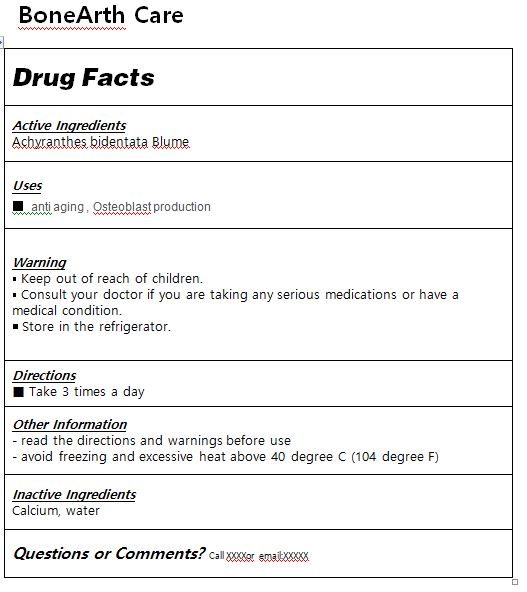 DRUG LABEL: BoneArth Care
NDC: 82230-0001 | Form: LIQUID
Manufacturer: Dong woo dang pharmacy Co.,Ltd.
Category: otc | Type: HUMAN OTC DRUG LABEL
Date: 20210910

ACTIVE INGREDIENTS: ACHYRANTHES BIDENTATA WHOLE 3 g/100 mL
INACTIVE INGREDIENTS: WATER

Drug Facts

ACTIVE INGREDIENT

Achyranthes bidentata Blume

PURPOSE

anti aging
Osteoblast production

KEEP OUT OF REACH OF THE CHILDREN

INDICATIONS AND USAGE

Take 3 times a day

WARNINGS

■ For external use only.

■ Do not use in eyes.

■ lf swallowed, get medical help promptly.

■ Stop use, ask doctor lf irritation occurs.

■ Keep out of reach of children.

DOSAGE AND ADMINISTRATION

for external use only

INACTIVE INGREDIENT

Water